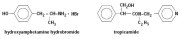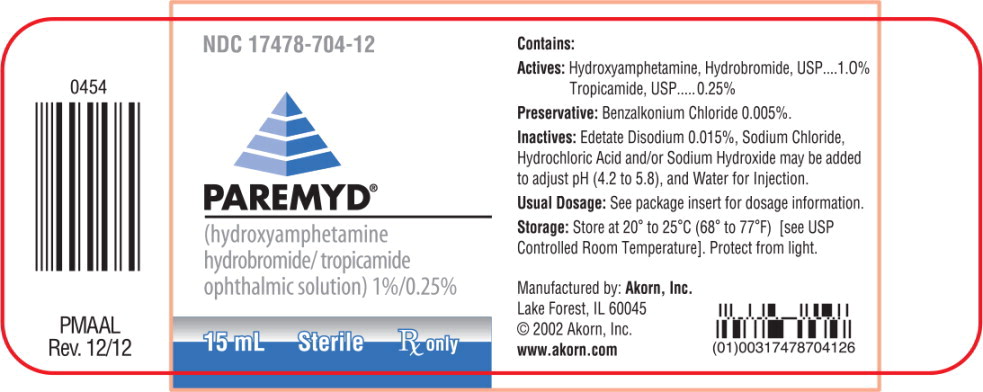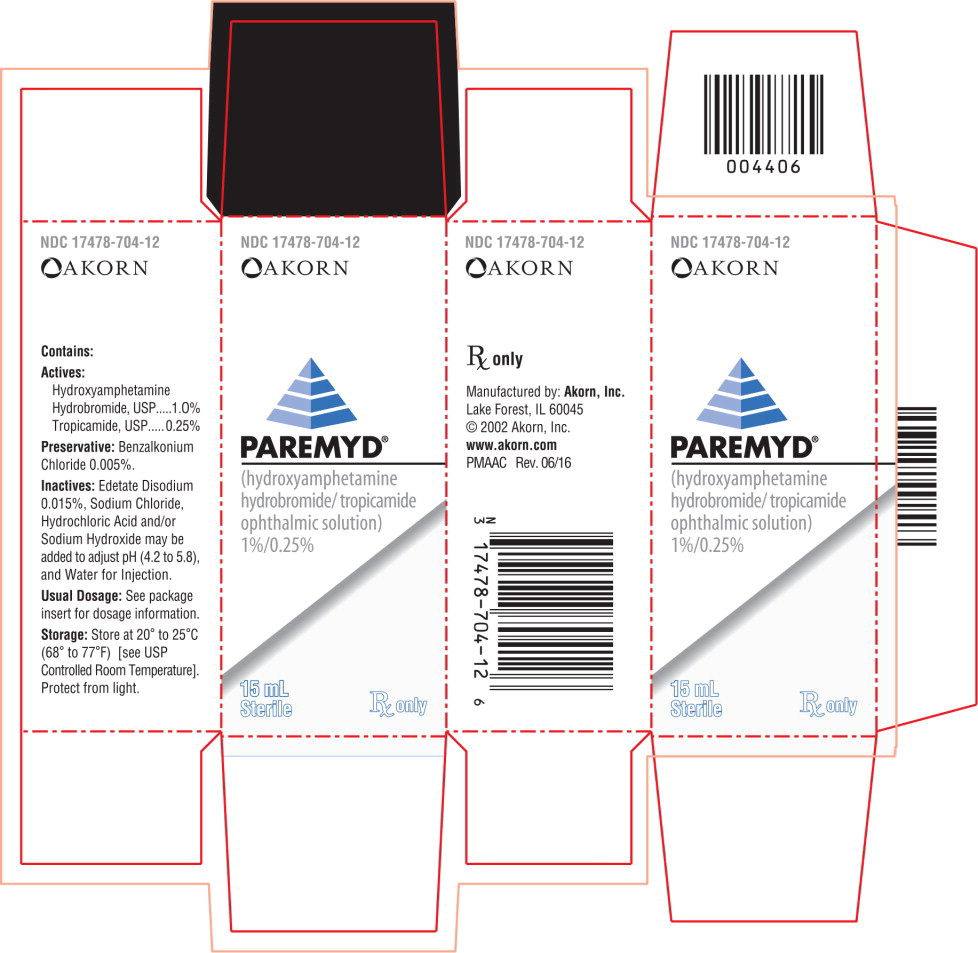 DRUG LABEL: Paremyd
NDC: 17478-704 | Form: SOLUTION
Manufacturer: Akorn
Category: prescription | Type: HUMAN PRESCRIPTION DRUG LABEL
Date: 20220914

ACTIVE INGREDIENTS: Hydroxyamphetamine hydrobromide 10 mg/1 mL; Tropicamide 2.5 mg/1 mL
INACTIVE INGREDIENTS: Edetate Disodium; Sodium Chloride; Hydrochloric Acid; Sodium Hydroxide; Water; Benzalkonium Chloride

PAREMYD®

1%/0.25%
Sterile

Rx only

DESCRIPTION

PAREMYD® sterile ophthalmic solution is a topical mydriatic combination product for ophthalmic use.

STRUCTURAL FORMULAE

CHEMICAL NAME
Hydroxyamphetamine hydrobromide: Phenol, 4-(2-aminopropyl)-, hydrobromide
Tropicamide: Benzeneacetamide, N-ethyl-α-(hydroxymethyl)-N-(4-pyridinylmethyl)-

CONTAINS
Actives: Hydroxyamphetamine hydrobromide, USP.......................1.0%
Tropicamide, USP.................................................................0.25%
Preservative: Benzalkonium Chloride 0.005%
Inactives: Edetate Disodium 0.015%, Sodium Chloride; Hydrochloric Acid and/or Sodium Hydroxide may be added to adjust pH (4.2 to 5.8 during its shelf life), and Water for Injecton. The osmolality of PAREMYD® is approximately 307 mOsm/l.

CLINICAL PHARMACOLOGY

PAREMYD® Solution combines the effects of the adrenergic agent, hydroxyamphetamine hydrobromide, and the anticholinergic agent, tropicamide.

Hydroxyamphetamine hydrobromide is an indirectly-acting sympathomimetic agent which, when applied topically to the eye, causes the release of endogenous norepinephrine from intact adrenergic nerve terminals resulting in mydriasis. Since hydroxyamphetamine hydrobromide has little or no direct activity on the receptor site, dilation does not usually occur if there is damage to the presynaptic nerve terminal, e.g., Horner's Syndrome. However, it is not known whether damage to the presynaptic nerve terminal will influence the extent of mydriasis produced by PAREMYD®. Hydroxyamphetamine hydrobromide has minimal cycloplegic action.

Tropicamide is a parasympatholytic agent which, when applied topically to the eye, blocks the responses of the sphincter muscle of the iris and the ciliary muscle to cholinergic stimulation, producing dilation of the pupil and paralysis of the ciliary muscle. Tropicamide produces short-duration mydriasis. Although cycloplegia occurs with higher doses of tropicamide, there is evidence with 0.25% tropicamide that full cycloplegia does not occur.

Since both these agents act on different effector sites, their simultaneous use produces an additive mydriatic effect. PAREMYD® provides diminished pupil responsiveness to light, facilitating ophthalmoscopy. The onset of action with PAREMYD® occurs within 15 minutes, followed by maximum effect within 60 minutes after instillation of one drop. Clinically significant dilation, inhibition of pupillary light response, and partial cycloplegia last 3 hours, with recovery beginning at approximately 90 minutes and with complete recovery occurring in most patients in 6 to 8 hours. However, in some cases complete recovery may take up to 24 hours. Effectiveness may differ slightly in patients with light and dark irides, with those patients with light irides experiencing a slightly greater mydriasis.

INDICATIONS

PAREMYD® Solution is indicated for mydriasis in routine diagnostic procedures and in conditions where short-term pupil dilation is desired. PAREMYD® provides clinically significant mydriasis with partial cycloplegia.

CONTRAINDICATIONS

PAREMYD® Solution should not be used in patients with angle-closure glaucoma or in those with narrow angles in whom dilation of the pupil may precipitate an attack of angle-closure glaucoma. This product is also contraindicated in patients who are hypersensitive to any of its components.

WARNINGS

For topical ophthalmic use only; not for injection.

There is evidence that mydriatics may produce a transient elevation of intraocular pressure in patients with open-angle glaucoma.

This preparation rarely may cause CNS disturbances which may be particularly dangerous in infants, children or the aged. Psychotic reactions, behavioral disturbances and vasomotor or cardio-respiratory collapse have been reported with the use of anticholinergic drugs.

PRECAUTIONS

General

Patients with hypertension, hyperthyroidism, diabetes or cardiac disease (i.e., arrhythmias or chronic ischemic heart disease) should be monitored after instillation. The elderly and others in whom glaucoma or increased intraocular pressure may be encountered following administration of PAREMYD® Solution should also be monitored closely. To avoid inducing angle-closure glaucoma, an estimation of the depth of the angle of the anterior chamber should be made.

Information for Patients

Patients should be advised not to touch the dropper tip to any surface since this may contaminate the solution. Patients should be advised to use caution when driving or engaging in other hazardous activities while pupils are dilated. Patients may experience photophobia and/or blurred vision and should protect their eyes in bright illumination when pupils are dilated. Parents should be warned not to get this preparation in their child's mouth and to wash their own hands and the child's hands following administration.

Carcinogenesis, mutagenesis, impairment of fertility

No studies have been performed to evaluate the carcinogenic, mutagenic or impairment of fertility potential of PAREMYD®.

Pregnancy

Pregnancy Category C

Animal reproduction studies have not been conducted with PAREMYD®. It is also not known whether PAREMYD® can cause fetal harm when administered to a pregnant woman or can affect reproduction capability. PAREMYD® should be given to a pregnant woman only if clearly needed.

Nursing Mothers

It is not known whether this drug is excreted in human milk. Because many drugs are excreted in human milk, caution should be exercised when PAREMYD® is administered to a nursing woman.

Pediatric Use

Safety and effectiveness in pediatric patients have not been established. PAREMYD® may rarely cause CNS disturbances which may be dangerous in infants and children. Psychotic reactions, behavioral disturbances and vasomotor or cardio-respiratory collapse in children have been reported with the use of anticholinergic drugs. (See WARNINGS). Keep this and all medications out of the reach of children.

Geriatric Use

No overall differences in safety or effectiveness have been observed between elderly and younger patients.

ADVERSE REACTIONS

Increased intraocular pressure has been reported following use of mydriatics. Transient stinging, dryness of the mouth, blurred vision, photophobia with or without corneal staining, tachycardia, headache, allergic reactions, nausea, vomiting, pallor and muscle rigidity have been reported with the use of tropicamide and/or hydroxyamphetamine hydrobromide, and thus may occur with PAREMYD® Solution. Central nervous system disturbances have also been reported. Psychotic reactions, behavioral disturbances, and vasomotor or cardiorespiratory collapse have been reported with the use of anticholinergic drugs.

Rare but serious cardiovascular events, including death due to myocardial infarction, ventricular fibrillation and significant hypotensive episodes have occurred shortly following PAREMYD® instillation.

OVERDOSAGE

Ocular overdosage will cause dilation of the pupils. Systemic overdosage or ingestion of large doses may result in hypertension, cardiac arrhythmias, sub-sternal discomfort, headache, sweating, nausea, vomiting and gastrointestinal irritation. Patients with systemic overdosage should be carefully monitored and treated symptomatically.

DOSAGE AND ADMINISTRATION

One to two drops in the conjunctival sac. The onset of action with PAREMYD® Solution occurs within 15 minutes followed by maximum effect within 60 minutes. Clinically significant dilation, inhibition of pupillary light response, and partial cycloplegia last 3 hours.

Mydriasis will reverse spontaneously with time, typically in 6 to 8 hours. However, in some cases, complete recovery may take up to 24 hours.

HOW SUPPLIED

PAREMYD® (hydroxyamphetamine hydrobromide/tropicamide ophthalmic solution) 1%/0.25% as a 15 mL solution in a 15 mL opaque white, low density polyethylene bottle with a natural low density polyethylene dropper tip and a red polypropylene cap.

15 mL - NDC 17478-704-12

STORAGE

Store at 20° to 25°C (68° to 77°F) [see USP Controlled Room Temperature]. Note: Protect from light.

Manufactured by:
Akorn, Inc.
Lake Forest, IL 60045

PM00N
Rev. 06/16

Container Label Principal Display Panel

NDC 17478-704-12

PAREMYD®

(hydroxyamphetamine

hydrobromide/tropicamide

ophthalmic solution) 1%/0.25%

15 mL Sterile Rx only

PACKAGE LABEL

Carton Principal Display Panel

NDC 17478-704-12

[Akorn logo]

PAREMYD®

(hydroxyamphetamine

hydrobromide/tropicamide

ophthalmic solution)

1%/0.25%

15 mL

Sterile Rx only